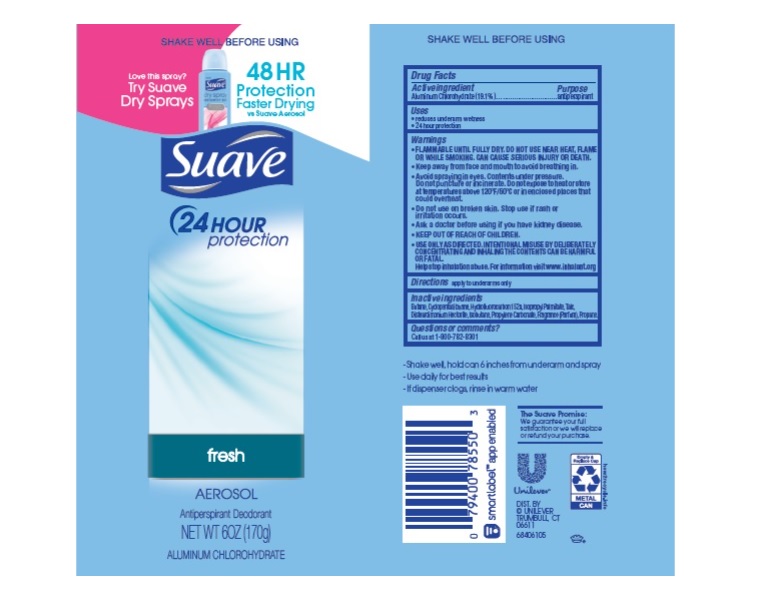 DRUG LABEL: Suave
NDC: 64942-1821 | Form: AEROSOL, SPRAY
Manufacturer: Conopco Inc. d/b/a/ Unilever
Category: otc | Type: HUMAN OTC DRUG LABEL
Date: 20230815

ACTIVE INGREDIENTS: ALUMINUM CHLOROHYDRATE 19.1 g/100 g
INACTIVE INGREDIENTS: BUTANE; CYCLOMETHICONE 5; 1,1-DIFLUOROETHANE; DISTEARDIMONIUM HECTORITE; ISOPROPYL PALMITATE; PROPYLENE CARBONATE; PROPANE; ISOBUTANE; TALC

Suave 24 Hour Protection Fresh Aerosol Antiperspirant Deodorant

SUAVE 24 HOUR PROTECTION FRESH AEROSOL ANTIPERSPIRANT DEODORANT - aluminum chlorohydrate aerosol, spray

Suave 24 Hour Protection Fresh Aerosol Antiperspirant Deodorant

Drug Facts

Active ingredient
Aluminum Chlorohydrate (19.1%)

Purpose

antiperspirant

Uses

reduces underarm wetness

24 hour protection

Warnings

• FLAMMABLE UNTIL FULLY DRY. DO NOT USE NEAR HEAT, FLAME, OR WHILE SMOKING. CAN CAUSE SERIOUS INJURY OR DEATH
• Keep away from face and mouth to avoid breathing in.
• Avoid spraying in eyes. Contents under pressure. Do not puncture or incinerate. Do not expose to heat or store at temperatures above 120°F/50°C or in enclosed places that could overheat
• Do not use on broken skin. Stop use if rash or irritation occurs.
• Ask a doctor before using if you have kidney disease.
• USE ONLY AS DIRECTED. INTENTIONAL MISUSE BY DELIBERATELY CONCENTRATING AND INHALING THE CONTENTS CAN BE HARMFUL OR FATAL.
Help stop inhalation abuse. For information visit www.inhalant.org

• KEEP OUT OF REACH OF CHILDREN.

Directions

FOR UNDERARM USE ONLY

Inactive ingredients

Butane, Cyclopentasiloxane, Hydrofluorocarbon 152a, Isopropyl Palmitate, Talc, Disteardimonium Hectorite, Isobutane, Propylene Carbonate, Fragrance (Parfum), Propane

Questions?

CCall us at 1-800-782-8301